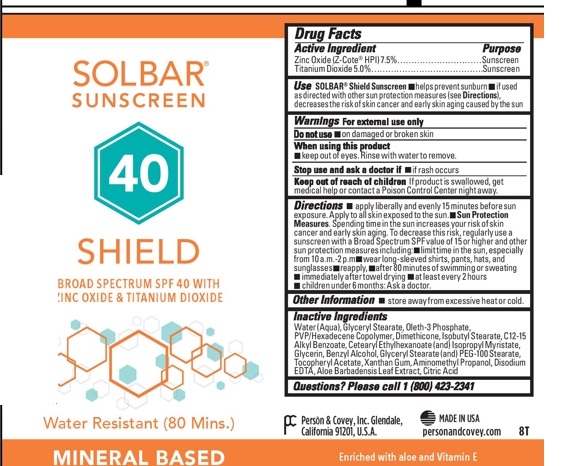 DRUG LABEL: Solbar Shield SPF40
NDC: 0096-0682 | Form: CREAM
Manufacturer: Person and Covey
Category: otc | Type: HUMAN OTC DRUG LABEL
Date: 20251204

ACTIVE INGREDIENTS: TITANIUM DIOXIDE 0.05 g/1 g; ZINC OXIDE 0.075 g/1 g
INACTIVE INGREDIENTS: GLYCERYL STEARATE SE; PEG-100 STEARATE; .ALPHA.-TOCOPHEROL, DL-; ANHYDROUS CITRIC ACID; XANTHAN GUM; EDETATE DISODIUM; ISOBUTYL STEARATE; CETEARYL ETHYLHEXANOATE; ISOPROPYL MYRISTATE; C12-20 ALKYL BENZOATE; ALOE VERA LEAF; WATER; GLYCERYL MONOSTEARATE; DIETHANOLAMINE OLETH-3 PHOSPHATE; DIMETHICONE; BENZYL ALCOHOL; GLYCERIN

Solbar Shield SP40

Indications and use

Helps prevent sunburn. If used as directed with other sun protection measures, decreases the risk of skin cancer and early skin aging caused by the sun. Dosage and Administration: Apply liberally and evenly to all sun exposed areas of DRY skin 15 minutes before sun exposure. Reapply after 80 minutes of swimming or sweating and immediately after towel drying. Apply at least every 2 hours. For children under 6 months, ask a physician.

Purpose

Sunscreen

Keep out of the reach of children

Yes. If swallowed, get medical help or contact a Poison Control Center right away.

Dosage and Administration

Apply liberally and evenly to all sun exposed areas of DRY skin 15 minutes before sun exposure. Reapply after 80 minutes of swimming or sweating and immediately after towel drying. Apply at least every 2 hours. For children under 6 months, ask a physician.

Warnings

For external use only. Do not use on damaged or broken skin. Keep out of eyes. Rinse eyes thoroughly with water to remove. Stop use and ask a physician if rash or irritation develops and lasts. Store away from excessive heat and direct sun.

OTC - ACTIVE INGREDIENT SECTION

Homosalate

Octinoxate

Oxybenzone

Avobenzone

INACTIVE INGREDIENT SECTION

Water

Isobutyl Stearate

Glycerin

Benzyl Alcohol

Simethicone

Cetyl Phosphate

Triethanolamine

Stearic Acid

Silica

Carbomer 1342

Acrylates/C10-30 Alkyl Acrylate Crosspolymer

Disodium EDTA